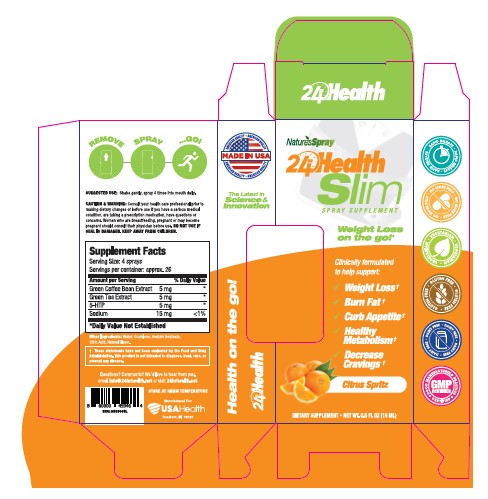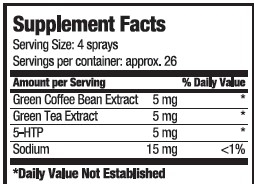 DRUG LABEL: 24hr Health Slim
NDC: 80893-006 | Form: SPRAY
Manufacturer: USA Health
Category: other | Type: Dietary Supplement
Date: 20201029

ACTIVE INGREDIENTS: SODIUM 15 mg/15 mL; GREEN TEA LEAF 5 mg/15 mL; ARABICA COFFEE BEAN 5 mg/15 mL; 5-HYDROXYTRYPTOPHAN, D- 5 mg/15 mL
INACTIVE INGREDIENTS: water; SUCRALOSE; SODIUM BENZOATE; CITRIC ACID MONOHYDRATE

24hr Health Slim

Purpose

Clinically formulated to help support

- Weight Loss
- Burn Fat
- Curb Appetite
- Healthy Metabolism
- Decrease Cravings

Precaution

Consult your health care professional prior to making dietary changes or before use if you have a serious medical condition, are taking a prescription medicine, have questions or concerns.

Warning

Women who are breastfeeding, pregnant, or may become pregnant should consult their physician before use.

Safe Handling

Do not use if damaged. Keep away from children.

Dosage

Shake gently. Spray 4 times into mouth daily.